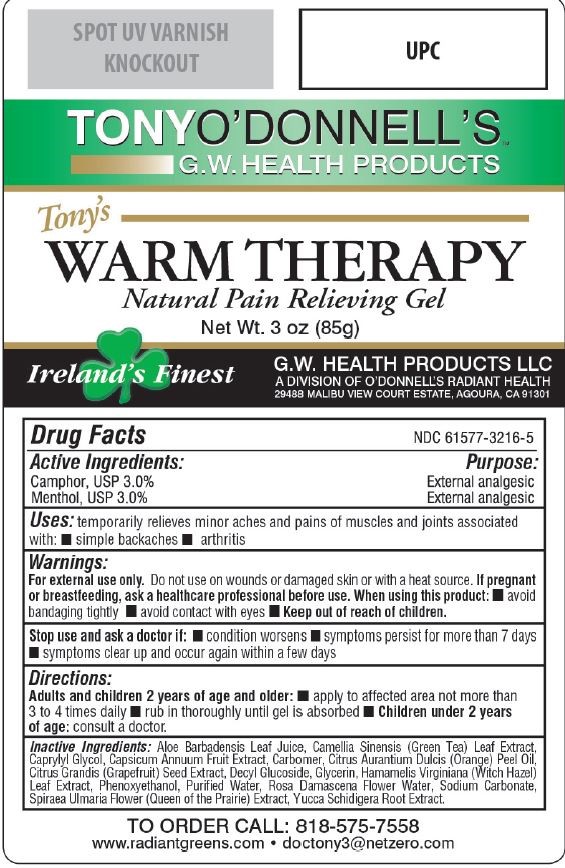 DRUG LABEL: Tonys Warm Therapy
NDC: 61577-1400 | Form: GEL
Manufacturer: Sombra Cosmetics
Category: otc | Type: HUMAN OTC DRUG LABEL
Date: 20210913

ACTIVE INGREDIENTS: MENTHOL 0.03 g/1 g; CAMPHOR (SYNTHETIC) 0.03 g/1 g
INACTIVE INGREDIENTS: ALOE VERA LEAF; CARBOMER HOMOPOLYMER TYPE C; DECYL GLUCOSIDE; WATER; CAPSAICIN; GRAPEFRUIT SEED OIL; GREEN TEA LEAF; FILIPENDULA ULMARIA FLOWER; ROSA CENTIFOLIA FLOWER OIL; SODIUM CARBONATE; GLYCERIN; WITCH HAZEL; YUCCA SCHIDIGERA ROOT; ORANGE PEEL; PHENOXYETHANOL; CAPRYLYL GLYCOL

Dr Tonys Warm Therapy

Active Ingredients

Menthol USP 3%, Camphor USP 3%

Purpose

External Analgesic

Keep out of reach of Children

Uses

Temporarily relieves minor arches and pains of muscles and joints associated with: arthritis, simple backaches.

warnings

For external use only. Do not use on wounds or damage skin. When using this product : avoid bandaging tightly, aviod contact with eyes, keep out of mreach of childern.

Stop use and ask doctor if : condition worsens, symptoms persist for more than 7 days, clear up and within a few days.

Directions

adults and childern 2 years of age and older: apply to affected area not more than 3 to 4 times daily, rub in thoroughtly until gel is absorbed, Childern under 2 years of age: consult a doctor.

Inactive Ingredients

aloe barbadensis leaf juice, carbomer, decyl glucoside, water, citrus grandis (grapefruit) seed extract, camellia sinensis (green tea) leaf extract, citrus aurantium dulcis (orange) peel oil, spiraea ulmaria flower (queen of the prairie) extract, rosa damascena flower water, sodium carbonate, glycerin, hamamelis virginiana (witch hazel) leaf extract, yucca schidigera root extract, phenoxyethanol, caprylyl glycol, capsicum annuum fruit extract

Questions or Comments

1-800-225-3963